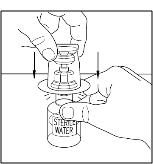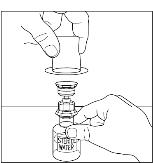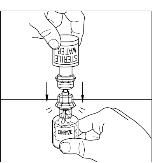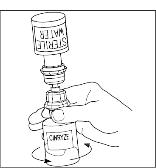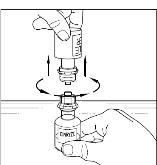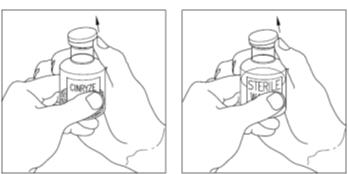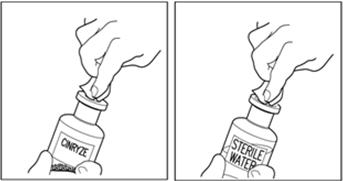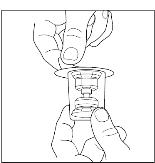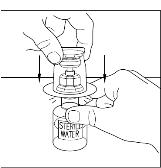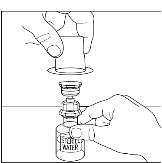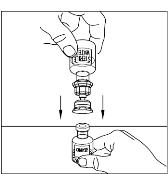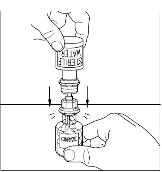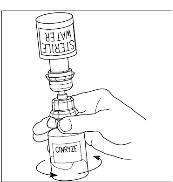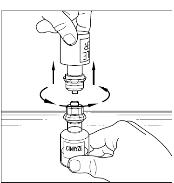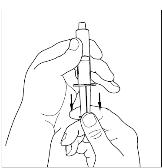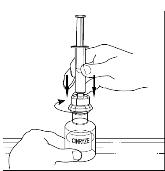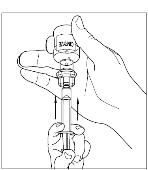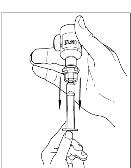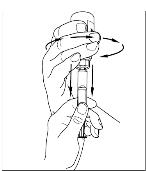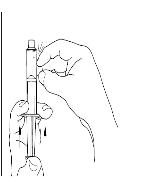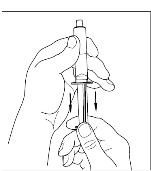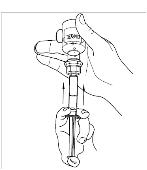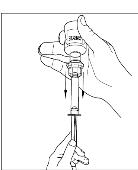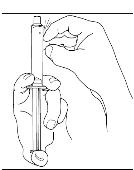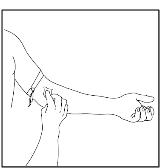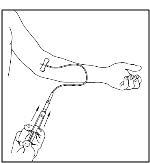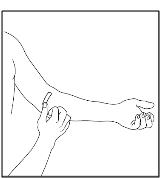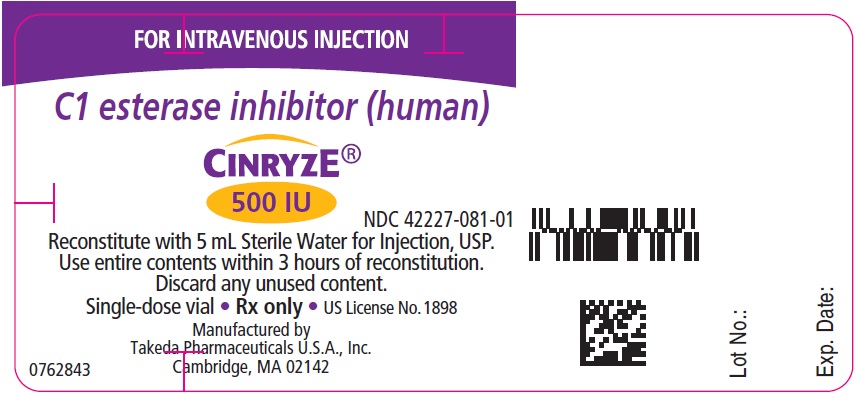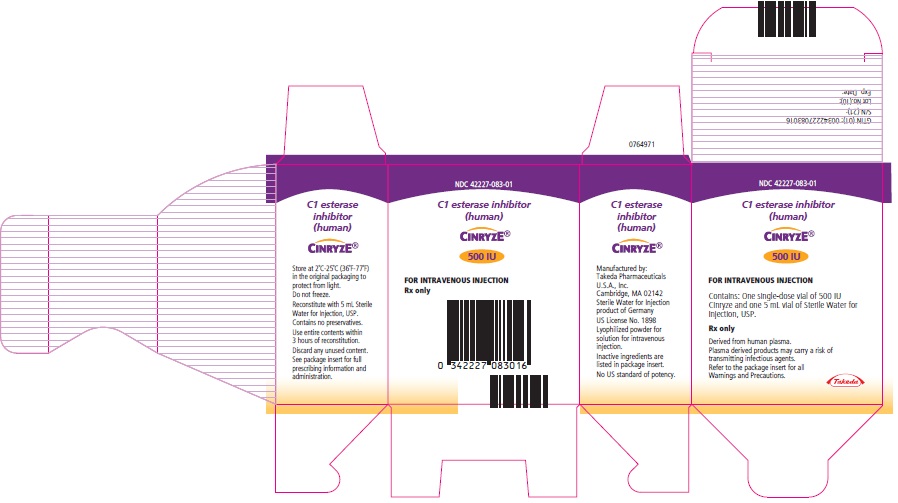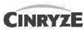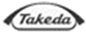 DRUG LABEL: Cinryze
NDC: 42227-081 | Form: INJECTION, POWDER, LYOPHILIZED, FOR SOLUTION
Manufacturer: Takeda Pharmaceuticals America, Inc.
Category: other | Type: PLASMA DERIVATIVE
Date: 20251128

ACTIVE INGREDIENTS: HUMAN C1-ESTERASE INHIBITOR 500 [iU]/5 mL
INACTIVE INGREDIENTS: SODIUM CHLORIDE; SUCROSE; TRISODIUM CITRATE DIHYDRATE; VALINE; ALANINE; THREONINE

HIGHLIGHTS OF PRESCRIBING INFORMATION

These highlights do not include all the information needed to use CINRYZE® safely and effectively. See full prescribing information for CINRYZE.
CINRYZE (C1 esterase inhibitor [human])
for intravenous use, freeze-dried powder for reconstitution
Initial U.S. Approval: 2008.

1 INDICATIONS AND USAGE

CINRYZE is a C1 esterase inhibitor indicated for routine prophylaxis against angioedema attacks in adults, adolescents, and pediatric patients (6 years of age and older) with Hereditary Angioedema (HAE). (1)

2 DOSAGE AND ADMINISTRATION

For Intravenous Use Only

- Prior to reconstitution, protect from light. (2.2)
- A silicone-free syringe is recommended. (2.2)
- Store at 36°F to 77°F (2°C to 25°C). Do not freeze. (16)
- To obtain a 500 International Units (IU) CINRYZE dose, reconstitute one CINRYZE vial with one vial of Sterile Water for Injection, USP (5 mL). To obtain a 1,000 IU CINRYZE dose, reconstitute two CINRYZE vials with two vials of Sterile Water for Injection, USP (5 mL each). Use aseptic sterile technique. (2.2)
- Administer at room temperature within 3 hours of reconstitution. (2.2)

Routine Prophylaxis Dosing (2.1)

Adults and adolescents (12 years old and above)

Indication | Dose | Infusion rate
Routine prophylaxis against HAE attacks | 1,000 IU Intravenous every 3 or 4 days [Doses up to 2,000 IU (not exceeding 80 IU/kg) every 3 or 4 days may be considered based on individual patient response.] | 1 mL/min (10 min)

Children (6 to 11 years old)

Indication | Dose | Infusion rate
Routine prophylaxis against HAE attacks | 500 IU Intravenous every 3 or 4 days [Doses up to 1,000 IU every 3 or 4 days may be considered based on individual patient response.] | 1 mL/min (5 min)

3 DOSAGE FORMS AND STRENGTHS

500 IU freeze-dried lyophilized powder in a single-dose vial for reconstitution with 5 mL of Sterile Water for Injection, USP. (3)

4 CONTRAINDICATIONS

Patients who have manifested life-threatening immediate hypersensitivity reactions, including anaphylaxis, to the product. (4)

5 WARNINGS AND PRECAUTIONS

- Hypersensitivity reactions may occur. Have epinephrine immediately available for treatment of acute severe hypersensitivity reaction (5.1)
- Serious arterial and venous thromboembolic (TE) events have been reported at the recommended dose of C1 esterase inhibitor (human) products, including CINRYZE, following administration in patients with HAE. Risk factors may include presence of an indwelling venous catheter/access device, prior history of thrombosis, underlying atherosclerosis, use of oral contraceptives, certain androgens, morbid obesity, and immobility. Benefits of CINRYZE for routine prophylaxis of HAE attacks should be weighed against the risks of TE events in patients with underlying risk factors. Monitor patients with known risk factors for TE events during and after CINRYZE administration. TE events have been reported following administration of a C1 esterase inhibitor (human) product when used off-label at higher than labeled doses. (5.2)
- CINRYZE is made from human plasma and may contain infectious agents e.g., viruses and, theoretically, the Creutzfeldt-Jakob disease agent. (5.3)

6 ADVERSE REACTIONS

The most common adverse reactions (≥5%) observed were headache, nausea, rash, vomiting, and fever. (6.1, 6.2)

To report SUSPECTED ADVERSE REACTIONS, contact Takeda Pharmaceuticals U.S.A., Inc. at 1-877-TAKEDA-7 (1-877-825-3327) or FDA at 1-800-FDA-1088 or www.fda.gov/medwatch.

FULL PRESCRIBING INFORMATION

1 INDICATIONS AND USAGE

CINRYZE is a C1 esterase inhibitor indicated for routine prophylaxis against angioedema attacks in adults, adolescents, and pediatric patients (6 years old and above) with Hereditary Angioedema (HAE).

2 DOSAGE AND ADMINISTRATION

For intravenous use only.

2.1 Dose

Table 1 Routine Prophylaxis Dosing in Adults, Adolescents, and Pediatric Patients.
Patient Population | Indication | Dose | Infusion Rate
Adults and adolescents (12 years old and above) | Routine prophylaxis against HAE attacks | 1,000 International Units (IU) [One International Unit (IU) corresponds to the amount of C1 esterase inhibitor present in 1 mL of normal plasma as defined by the WHO international reference standard. Previously, the potency values were expressed in Units (U) and were relative to an in-house reference standard. A conversion factor of 0.83 can be used to recalculate the potency from U to IU, i.e., 100 U = 83 IU. The data that were generated with CINRYZE expressed in Units, are not converted to IU in the Prescribing Information.] Intravenous (IV) every 3 or 4 days. For patients who have not responded adequately, doses up to 2,000 IU (not exceeding 80 IU/kg) every 3 or 4 days may be considered based on individual patient response. | 1 mL/min (10 min)
Pediatric patients (6 to 11 years old) | Routine prophylaxis against HAE attacks | 500 IU, Intravenous (IV) every 3 or 4 days. The dose may be adjusted according to individual response, up to 1,000 IU every 3 or 4 days. | 1 mL/min (5 min)

2.2 Preparation

- Protect CINRYZE from light prior to reconstitution.
- A silicone-free syringe is recommended for reconstitution and administration of CINRYZE.
- Inspect the reconstituted product for particulate matter prior to administration; do not use if particles are observed or if solution is turbid. The reconstituted solution is colorless to slightly blue.
- Each vial of CINRYZE is for single use only. Promptly use any vial that has been entered and discard partially used vials in accordance with biohazard procedures. CINRYZE contains no preservative.
- Do not mix CINRYZE with other materials.
- Do not use if frozen.
- Do not use after expiration date.
- Use aseptic technique during the reconstitution procedure.
- Bring the CINRYZE (powder) and Sterile Water for Injection, USP (diluent) to room temperature if refrigerated.
- Remove caps from the CINRYZE and diluent vials.
- Cleanse stoppers with an alcohol wipe or swab and allow them to dry prior to use.
- Remove protective covering from the top of the Mix2Vial transfer device package. Do not remove the device from the package.
- Note: Diluent vial must be accessed prior to the vial of CINRYZE to prevent loss of vacuum.

Reconstitution

Sterile Water for Injection USP is required for reconstitution. CINRYZE is supplied with Sterile Water for Injection USP [see How Supplied/Storage and Handling (16)].

One vial of reconstituted CINRYZE is used for a single 500 IU dose. Two vials of reconstituted CINRYZE are combined for a single 1,000 IU dose.

1. Place diluent on a flat surface and insert the blue end of the device into the diluent vial, pushing down until the spike penetrates through the center of the diluent vial stopper and the device snaps in place (Figure 1). The Mix2Vial transfer device must be positioned completely vertical prior to penetrating the stopper closure.
  Figure 1
2. Remove the plastic package and discard it (Figure 2). Take care not to touch the exposed end of the device.
  Figure 2
3. Place vial of CINRYZE on a flat surface. Invert diluent vial containing 5 mL of Sterile Water for Injection, USP, and insert the clear end into the CINRYZE vial, pushing down until the spike penetrates the rubber stopper and the device snaps into place. The Mix2Vial transfer device must be positioned completely vertical prior to penetrating the stopper closure. The Sterile Water for Injection, USP will automatically flow into the vial of CINRYZE (Figure 3), because the vacuum in the vial will draw in the diluent. If there is no vacuum in the vial, do not use the product.
  Figure 3
4. Gently swirl (do not shake) the CINRYZE vial until all powder is dissolved. Be sure that CINRYZE is completely dissolved (Figure 4).
  Figure 4
5. Disconnect the Sterile Water for Injection, USP vial by turning it counterclockwise (Figure 5). Do not remove the clear end of the Mix2Vial transfer device from the vial of CINRYZE.
  Figure 5

One vial of reconstituted CINRYZE contains 5 mL of C1 esterase inhibitor at a concentration of 100 IU/mL. Reconstitute one vial of CINRYZE for one 500 IU dose. Reconstitute two vials of CINRYZE for one 1,000 IU dose. Repeat steps 1 to 5 above using an additional package containing a Mix2Vial transfer device to reconstitute the second of two vials of CINRYZE. Do not reuse the Mix2Vial transfer device. CINRYZE must be administered at room temperature within 3 hours after reconstitution. For higher doses up to 2,000 IU (not exceeding 80 IU/kg) additional vial(s) will need to be reconstituted.

2.3 Administration

The procedures below are provided as general guidelines for the reconstitution and administration of CINRYZE. Use either the Mix2Vial® transfer device or a commercially available double-ended needle.

Always work on a clean surface and wash your hands before performing the following procedures.

Reconstitution, product administration, and handling of the administration set, and needles must be done with caution. Percutaneous puncture with a needle contaminated with blood can transmit infectious viruses including HIV (AIDS) and hepatitis. Obtain immediate medical attention if injury occurs. Place needles in a sharps container after single use. Discard all equipment, including any reconstituted CINRYZE, in an appropriate container.

One vial of reconstituted CINRYZE is used for a single 500 IU dose.

Two vials of reconstituted CINRYZE are combined for a single 1,000 IU dose.

For higher doses of up to 2,000 IU, combine the contents of the relevant number of vials.

Instructions for Use

1. Use aseptic technique.
2. After reconstitution, the solution should be clear with no evidence of turbidity. Reconstituted solution should be colorless to slightly blue. Do not use if solution is turbid or otherwise discolored.
3. Please refer to the illustrations in steps 7 to 9 included within the Patient Information Leaflet. Utilizing a sterile, disposable 10 mL syringe, draw back the plunger to admit 5 mL air into the syringe.
4. Attach the syringe onto the top of the clear end of the Mix2Vial transfer device by turning it clockwise.
5. Invert the vial and inject air into the solution and then slowly withdraw the reconstituted CINRYZE into the syringe.
6. Detach the syringe from the vial by turning it counterclockwise and releasing it from the clear end of the Mix2Vial transfer device.
7. For a 1,000 IU dose, using the same syringe, repeat steps 3 to 6 with a second vial of CINRYZE to make the complete dose.
8. Promptly administer CINRYZE after preparation in the syringe and do not use if particles are observed or if the solution is turbid.
9. Attach a suitable needle or infusion set with winged adapter and inject intravenously. As a guideline, administer CINRYZE by intravenous injection at a rate of 1 mL per minute. A single dose of 500 IU (reconstituted in 5 mL) of CINRYZE should be administered over 5 minutes. A single dose of 1,000 IU (reconstituted in 10 mL) of CINRYZE should be administered over 10 minutes. [see Dosage and Administration (2)]. Please refer to the illustration in step 3 of the self-administration section within the Patient Information Leaflet.
10. Dispose of all unused solution, the empty vial(s), and the used needles and syringes in an appropriate container for throwing away waste that might hurt others if not handled properly.

3 DOSAGE FORMS AND STRENGTHS

- CINRYZE (Freeze-Dried powder for Reconstitution) is a lyophilized preparation available in a single-dose vial that contains 500 IU human C1 esterase inhibitor.
- Each vial must be reconstituted with 5 mL of Sterile Water for Injection, USP (diluent).
- One reconstituted vial must be used to make a single, 500 IU, dose. Two reconstituted vials must be used to make a single, 1,000 IU dose.

4 CONTRAINDICATIONS

CINRYZE is contraindicated in patients who have manifested life-threatening immediate hypersensitivity reactions, including anaphylaxis, to the product.

5 WARNINGS AND PRECAUTIONS

5.1 Hypersensitivity Reactions

Severe hypersensitivity reactions may occur. The signs and symptoms of hypersensitivity reactions may include the appearance of hives, urticaria, tightness of the chest, wheezing, hypotension and/or anaphylaxis experienced during or after injection of CINRYZE.

Consider treatment methods carefully because hypersensitivity reactions may have symptoms similar to HAE attacks.

In case of hypersensitivity, discontinue CINRYZE infusion and institute appropriate treatment. Have epinephrine immediately available for treatment of acute severe hypersensitivity reaction. [see Patient Counseling Information (17)].

5.2 Thromboembolic Events

Serious arterial and venous thromboembolic (TE) events have been reported at the recommended dose of C1 esterase inhibitor (human) products, including CINRYZE, following administration in patients with HAE. Risk factors may include presence of an indwelling venous catheter/access device, prior history of thrombosis, underlying atherosclerosis, use of oral contraceptives, certain androgens, morbid obesity, and immobility. Benefits of CINRYZE for routine prophylaxis of HAE attacks should be weighed against the risks of TE events in patients with underlying risk factors. Monitor patients with known risk factors for TE events during and after CINRYZE administration.

TE events have been reported following administration of a C1 esterase inhibitor (human) product when used off-label at higher than labeled doses^1.

In an open-label trial further investigating the use of CINRYZE for prevention (n=146) of HAE attacks, 5 serious TE events (including myocardial infarction, deep vein thrombosis, pulmonary embolism and 2 events of cerebrovascular accident) occurred. Subjects had underlying risk factors for TE events.

In the post-approval open-label study (n=20) there were no systemic TE events in subjects who received CINRYZE up to 2,500 U (not exceeding 100 U/kg) every 3 or 4 days for up to 12 months. One subject developed a blood clot in an intravenous central catheter, which was treated without systemic complication. [see Adverse Reactions (6.1)].

5.3 Transmissible Infectious Agents

Because CINRYZE is made from human blood, it may carry a risk of transmitting infectious agents, e.g., viruses, and, theoretically, the Creutzfeldt-Jakob disease (CJD) agent [see Description (11)]. ALL infections thought by a physician possibly to have been transmitted by CINRYZE should be reported by the physician or other healthcare provider to Takeda Pharmaceuticals U.S.A., Inc. [1-877-TAKEDA-7 (1-877-825-3327)]. The physician should discuss the risks and benefits of this product with the patient, before prescribing or administering it to the patient. [see Patient Counseling Information (17)]

6 ADVERSE REACTIONS

The most common adverse reactions (≥5%) observed were headache, nausea, rash, vomiting, and fever.

6.1 Clinical Trials Experience

Because clinical studies are conducted under widely varying conditions, adverse reaction rates observed in the clinical trials of a drug cannot be directly compared to rates in the clinical trials of another drug and may not reflect the rates observed in practice.

Twenty-four subjects age 9 to 73 years old were evaluated in the randomized, placebo-controlled, crossover, routine prophylaxis trial. There were no serious adverse reactions in the randomized, placebo-controlled, crossover, routine prophylaxis trial.

Adverse reactions in the randomized, placebo-controlled, crossover, routine prophylaxis trial (n=24) that occurred in at least two subjects (≥8%) receiving CINRYZE are given in Table 2:

Table 2 Adverse Reactions in the Randomized, Placebo-Controlled, Crossover, Routine Prophylaxis Trial.
Adverse Reaction | Number of Adverse Reactions | Number of Subjects (N = 24)
Rash | 8 | 5
Headache | 4 | 4
Pruritus | 2 | 2
Vomiting | 2 | 2

In an open-label follow-on trial, 146 subjects age 3 to 82 years old received a median of 243.5 days of CINRYZE (maximum = 959 days). The most common adverse reaction observed was headache. No subjects were discontinued due to an adverse reaction.

Adverse reactions in the open-label follow-on trial (n=146) that occurred in at least three subjects (≥2%) receiving CINRYZE, are given in Table 3:

Table 3 Adverse Reactions in the Open-Label Follow-On Trial.
Adverse Reaction | Number (%) of Subjects (N=146) with Adverse Reaction | Number (%) of Infusion Days (N=11,435) with Adverse Reaction
Headache | 28 (19) | 62 (0.5)
Nausea | 26 (18) | 29 (0.3)
Rash | 15 (10) | 30 (0.3)
Vomiting | 15 (10) | 17 (0.1)
Pyrexia (fever) | 7 (5) | 7 (<0.1)
Catheter Site Pain | 4 (3) | 5 (<0.1)
Dizziness | 3 (2) | 4 (<0.1)
Erythema | 3 (2) | 3 (<0.1)
Pruritus | 3 (2) | 4 (<0.1)

Serious adverse reactions included cerebrovascular accident [see Warnings and Precautions (5.2)].

Twelve pediatric subjects age 7 to 11 years old were evaluated in a randomized, dose-ranging, crossover routine prophylaxis trial (500 U and 1,000 U). No new adverse reactions (compared to the placebo-controlled routine prophylaxis trial or the open label follow-on trial) were identified. The adverse reactions among the pediatric subjects were headache, nausea, pyrexia (fever), and infusion site erythema. None of these adverse reactions were severe, and none led to discontinuation of CINRYZE. The safety profile with 500 U or 1,000 U of CINRYZE treatment was comparable. Overall, the safety and tolerability of CINRYZE are similar in pediatric, adolescent, and adult subjects.

More than 14,000 doses of CINRYZE have been administered to over 260 different subjects in all completed, controlled and open-label clinical studies. All subjects who were evaluated were found negative for seroconversion to parvovirus B19, Hepatitis B, Hepatitis C and HIV. [see Warnings and Precautions (5.3)]

A post-approval open-label study assessed escalating doses of CINRYZE (1,500 U, 2,000 U, 2,500 U every 3 or 4 days) as prophylactic therapy in 20 subjects who had an inadequate response (> 1.0 HAE attack/month, regardless of severity) to 1,000 U every 3 or 4 days. The safety profile of doses up to 2,500 U was consistent with previous clinical trial experience at lower doses.

6.2 Immunogenicity

Because CINRYZE is a therapeutic protein, there is potential for immunogenicity. The detection of antibody formation is highly dependent on the sensitivity and specificity of the assay. Additionally, the observed incidence of anti-C1 esterase inhibitor antibody positivity in an assay may be influenced by several factors including assay methodology, sample handling, timing of sample collection, concomitant medications, and underlying disease. For these reasons, comparison of the incidence of antibody development across products cannot be made.

6.3 Postmarketing Experience

Because post marketing reporting of adverse reactions is voluntary and from a population of uncertain size, it is not always possible to reliably estimate the frequency of these reactions or establish a causal relationship to product exposure.

Postmarketing adverse reactions included local infusion site reactions (including inflammation or hematoma at the infusion site) and hypersensitivity.

8 USE IN SPECIFIC POPULATIONS

8.1 Pregnancy

Risk Summary

There are no data with CINRYZE use in pregnant women to inform a drug associated risk. Animal reproduction studies have not been conducted with CINRYZE. It is unknown whether CINRYZE can cause fetal harm when administered to a pregnant woman or can affect reproduction capacity. CINRYZE should be given to a pregnant woman only if clearly needed.

In the U.S. general population, the estimated background risk of major birth defects and miscarriage in clinically recognized pregnancies is 2 to 4% and 15 to 20%, respectively.

Data

Animal data

In an embryo fetal development study (C1 inhibitor administered during the period of organogenesis) in rats, there was no maternal or fetal toxicity at doses up to 400 U/kg/day that provided an exposure similar to that in humans after a 1,000 U dose.

8.2 Lactation

Risk Summary

There are no data regarding the presence of CINRYZE in human milk, the effects on the breastfed infant, or the effects on milk production. The developmental and health benefits of breastfeeding should be considered along with the mother's clinical need for CINRYZE and any potential adverse effects on the breastfed child from CINRYZE or from the underlying maternal condition.

8.4 Pediatric Use

The safety and effectiveness of CINRYZE have been evaluated in 12 pediatric subjects with HAE (age range 7 to 11 years old) in a pediatric randomized, dose-ranging, crossover routine prophylaxis trial. [see Clinical Studies (14)]. Additionally, four of the 24 subjects in the pediatric/adult randomized, placebo-controlled, crossover, routine prophylaxis trial, were under the age of 18 years (9, 14, 16, and 17 years of age). Overall, the safety and tolerability of CINRYZE are similar in pediatric, adolescent, and adult subjects. The pharmacokinetics of CINRYZE was evaluated in pediatric subjects (7 to 11 years old). [see Clinical Pharmacology (12)].

8.5 Geriatric Use

Clinical studies of CINRYZE did not include sufficient numbers of subjects aged 65 and over to determine whether they respond differently from younger subjects. Other reported clinical experience has not identified differences in responses between the elderly and younger patients. In general, dose selection for an elderly patient should be cautious, usually starting at the low end of the dosing range, reflecting the greater frequency of decreased hepatic, renal, or cardiac function, and of concomitant disease or other drug therapy.

10 OVERDOSAGE

The maximum dose administered in clinical studies was 4,000 U given over approximately 4 hours and 10,000 U given over a 7-day period. There have been no overdosages of CINRYZE reported during clinical studies.

11 DESCRIPTION

CINRYZE (C1 esterase inhibitor [human]) (Freeze-Dried Powder for Reconstitution) is a sterile, stable, lyophilized preparation of C1 esterase inhibitor derived from human plasma. CINRYZE is manufactured from human plasma purified by a combination of filtration and chromatographic procedures. CINRYZE potency is expressed by its C1 esterase inhibitor activity measured with a validated chromogenic assay. The potency of C1 esterase inhibitor is expressed in International Units (IU), which is related to the current WHO standard for C1 esterase inhibitor products. One International Unit (IU) corresponds to the amount of C1 esterase inhibitor present in 1 mL of normal plasma.

The specific activity of CINRYZE is 4.0 to 9.0 U/mg protein. The purity is ≥90% human C1 esterase inhibitor. Following reconstitution with 5 mL of Sterile Water for Injection, USP, each vial contains approximately 500 IU of functionally active C1 esterase inhibitor, pH 6.6 to 7.4, and an osmolality between 200 to 400 mosmol/kg.

CINRYZE, when reconstituted with 5 mL of Sterile Water for Injection, USP contains the following excipients: 4.1 mg/mL sodium chloride, 21 mg/mL sucrose, 2.6 mg/mL trisodium citrate, 2.0 mg/mL L-Valine, 1.2 mg/mL L-Alanine, and 4.5 mg/mL L-Threonine.

The following manufacturing steps are designed to reduce the risk of viral transmission:

- Screening donors at U.S. licensed blood collection centers to rule out infection with Human Immunodeficiency Virus (HIV-1/HIV-2), Hepatitis B Virus, or Hepatitis C Virus.
- Testing plasma pools by in-process NAT for parvovirus B19 via minipool testing and the limit of B19 in the manufacturing pool is set not to exceed 10^4 IU of B19 DNA per mL.
- Use of two independent viral reduction steps in the manufacture of CINRYZE: pasteurization (heat treatment at 60°C for 10 hours in solution with stabilizers) and nano filtration through two sequential 15 nm filters.

These viral reduction steps, along with a step in the manufacturing process, PEG precipitation, have been validated in a series of in vitro experiments for their capacity to inactivate/remove a wide range of viruses of diverse physicochemical characteristics including: Human Immunodeficiency Virus (HIV), Hepatitis A Virus (HAV), and the following model viruses: Bovine Viral Diarrhea Virus (BVDV) as a model virus for HCV, Canine Parvovirus (CPV) as a model virus for Parvovirus B19, Pseudorabies Virus (PRV) as a model virus for large enveloped DNA viruses (e.g. herpes virus). Total mean log10 reductions are shown in Table 4.

Table 4 Log10 Virus Reduction Factor for Selected Viruses.
Process Step | Enveloped Viruses - HIV | Enveloped Viruses - BVDV | Enveloped Viruses - PRV | Non-enveloped Viruses - HAV | Non-enveloped Viruses - CPV
PEG precipitation | 5.1 ± 0.2 | 4.5 ± 0.3 | 6.0 ± 0.3 | 2.8 ± 0.2 | 4.2 ± 0.2
Pasteurization | > 6.1 ± 0.2 | > 6.7 ± 0.3 | > 6.7 ± 0.2 | 2.8 ± 0.3 | 0.1 ± 0.3
Nano filtration | > 5.6 ± 0.2 | > 5.5 ± 0.2 | > 6.4 ± 0.3 | > 4.9 ± 0.2 | > 4.5 ± 0.3
Total reduction | > 16.8 | > 16.7 | > 19.1 | > 10.5 | > 8.7

12 CLINICAL PHARMACOLOGY

12.1 Mechanism of Action

C1 inhibitor is a normal constituent of human blood and is one of the serine proteinase inhibitors (serpins). The primary function of C1 inhibitor is to regulate the activation of the complement and intrinsic coagulation (contact system) pathway. C1 inhibitor also regulates the fibrinolytic system. Regulation of these systems is performed through the formation of complexes between the proteinases and the inhibitor, resulting in inactivation of both and consumption of the C1 inhibitor.

HAE patients have low levels of endogenous or functional C1 inhibitor. Although the events that induce attacks of angioedema in HAE patients are not well defined, it is thought by some that increased vascular permeability and the clinical manifestation of HAE attacks are primarily mediated through contact system activation. Suppression of contact system activation by C1 inhibitor through the inactivation of plasma kallikrein and factor XIIa is thought to modulate this vascular permeability by preventing the generation of bradykinin^2. Administration of CINRYZE increases plasma levels of C1 inhibitor activity.

12.2 Pharmacodynamics

In clinical studies, the intravenous administration of CINRYZE demonstrated an increase in plasma levels of C1 inhibitor within approximately one hour or less of administration.

Biological activity of CINRYZE was shown in 35 subjects by the subsequent increase in plasma C4 levels from an average of C4 8.1 mg/dL at baseline to C4 8.6 mg/dL 12 hours after infusion of CINRYZE. Pharmacodynamics was investigated in children 7 to 11 years old following IV administration of two dose levels of CINRYZE (500 U and 1,000 U) every 3 or 4 days for 12 weeks to prevent angioedema attacks. C4 levels increased from an average of 6.80 mg/dL at baseline to 7.92 mg/dL for the 500 U dose, and to 9.27 mg/dL for the 1,000 U dose, measured one hour after the final administered dose of the 12-week treatment period.

12.3 Pharmacokinetics

A randomized, parallel group, open-label pharmacokinetics (PK) study of CINRYZE was performed in subjects with non-symptomatic hereditary angioedema (HAE). The subjects received either a single dose of 1,000 U or 1,000 U followed by a second 1,000 U 60 minutes later. The PK results for functional C1 inhibitor are presented in the Table 5.

Table 5 Mean Pharmacokinetic Parameters of Functional C1 Inhibitor.
Parameters | Single Dose [Single dose = 1,000 Units] | Double Dose [Double dose = 1,000 Units followed by a second 1,000 Units 60 minutes later]
Cbaseline (U [One Unit is equal to the mean C1 inhibitor concentration of 1 mL of normal human plasma] /mL) | 0.31 ± 0.20 (n [Numbers in parentheses are number of subjects evaluated] = 12) | 0.33 ± 0.20 (n = 12)
Cmax (U/mL) | 0.68 ± 0.08 (n = 12) | 0.85 ± 0.12 (n = 13)
Tmax (hrs) | 3.9 ± 7.3 (n = 12) | 2.7 ± 1.9 (n = 13)
AUC(0-t) (U hr/mL) | 74.5 ± 30.3 (n = 12) | 95.9 ± 19.6 (n = 13)
CL (mL/min) | 0.85 ± 1.07 (n = 7) | 1.17 ± 0.78 (n = 9)
Half-life (hours) | 56 ± 36 (n = 7) | 62 ± 38 (n = 9)

The maximum plasma concentration (Cmax) and area under the plasma concentration-time curve (AUC) increased from the single to double dose, although the increase was not dose proportional. The mean half-lives of CINRYZE were 56 hours (range 11 to 108 hours) for a single dose and 62 hours (range 16 to 152 hours) for the double dose.

Pharmacokinetics was investigated in children 7 to 11 years old following IV administration of two dose levels of CINRYZE (500 U and 1,000 U) every 3 or 4 days for 12 weeks to prevent angioedema attacks. At one-hour post-dose during the steady state (Week 12), mean (SD) C1 inhibitor functional activities were 0.53 (0.13) U/mL, and 0.81 (0.20) U/mL, following IV administration of 500 U and 1,000 U CINRYZE, respectively, increasing from the baseline value of 0.18 (0.10) U/mL.

Population PK modelling was conducted to evaluate the exposure in a pediatric population compared with adults. The PK parameters for functional C1 inhibitor in pediatrics (7 to 11 years) are presented in Table 6. Following dosing every 3 to 4 days with 1,000 U, mean AUC0-4 and Cmax were approximately 30% higher in children 7 to 11 years old than in adults who received 1,000 U.

Table 6 Mean (SD) Steady State PK Parameters of Functional C1 Inhibitor in Pediatrics (7 to 11 years).
Parameters | 500 U (n=12) | 1,000 U (n=13)
Cmax,ss (U/mL) | 0.53 (0.11) | 0.89 (0.18)
Cmin,ss (U/mL) | 0.26 (0.08) | 0.34 (0.11)
AUCtau,ss (U∙hr/mL) | 30.10 (7.57) | 45.10 (10.9)
AUC0-4,ss (U∙hr/mL) | 2.06 (0.42) | 3.40 (0.68)
CL (mL/min) | 0.67 (0.23) | 0.67 (0.22)
Half-life (hours) | 34.60 (6.72) | 34.10 (6.67)
AUC0-4,ss = area under the concentration-time curve from time 0 to 4 h at steady state; AUCtau,ss = area under the concentration-time curve over the dosing interval at steady state; Cmax,ss = maximum concentration at steady state; Cmin,ss = minimum pre-dose concentration at steady state; CL: Clearance.

Studies have not been conducted to evaluate the PK of CINRYZE in special patient populations identified by gender, race, geriatric age, or the presence of renal or hepatic impairment.

13 NONCLINICAL TOXICOLOGY

13.1 Carcinogenesis, Mutagenesis, Impairment of Fertility

No animal studies have been completed to evaluate the effects of CINRYZE on carcinogenesis, mutagenesis, and impairment of fertility.

13.2 Animal Toxicology and/or Pharmacology

Acute toxicity of CINRYZE was studied in a combined acute toxicity and 7-day repeat dose/ dose range finding (DRF) study in Sprague Dawley rats followed by a pivotal 14-day repeat dose study. The acute and 14-day repeat dose toxicity studies were performed with intravenous administration of CINRYZE at dose levels of 1, 7- and 28-times normal dose. No signs of toxicity were observed in the single dose or repeat dose studies. Repeat dosing in the rat resulted in an antibody response between days 1 and 14 that was not characterized for neutralizing activity. However, there was no change in the functional activity of CINRYZE over the dosing period.

In vitro and in vivo animal thrombogenicity studies with CINRYZE showed a potential for clot formation when CINRYZE was administered at doses 14 times the recommended clinical dose (greater than 200 U/kg). Animal studies have supported a concern about the risk of thrombosis from intravenous administration of C1 esterase inhibitor products. [see Warnings and Precautions (5.2)].

14 CLINICAL STUDIES

The safety and efficacy of CINRYZE prophylaxis therapy to reduce the incidence, severity, and duration of HAE attacks was demonstrated in a single randomized, double blind, placebo controlled multicenter cross-over study of 24 subjects. Subjects were screened to confirm a diagnosis of HAE and a history of at least two HAE attacks per month. 24 subjects (mean age 38.1 years with a range of 9 to 73 years) were randomized to one of two treatment groups: either CINRYZE prophylaxis for 12 weeks followed by 12 weeks of placebo prophylaxis; or randomized to placebo prophylaxis for 12 weeks followed by 12 weeks of CINRYZE prophylaxis. Two subjects dropped out (one in each arm); 22 subjects crossed over into period 2 and were included in the efficacy analysis. Subjects were given blinded injections (CINRYZE or placebo) every 3 to 4 days, approximately 2 times per week. Subjects recorded all angioedema symptoms daily. An attack was defined as the subject-reported indication of swelling at any location following a report of no swelling on the previous day.

The efficacy determination was based on the number of attacks during the 12-week period while receiving CINRYZE as compared to the number of attacks during the placebo treatment period. The effectiveness of C1 esterase inhibitor prophylaxis in reducing the number of HAE attacks was variable among the subjects as shown in Table 7, Table 8, and Table 9.

Table 7 Prevention of HAE Attacks by Subject in the Randomized, Placebo-Controlled, Crossover, Routine Prophylaxis Trial.
Subject | Percent Reduction in Attack Frequency
1 | 100%
2 | 100%
3 | 100%
4 | 100%
5 | 90%
6 | 88%
7 | 84%
8 | 83%
9 | 78%
10 | 76%
11 | 60%
12 | 47%
13 | 43%
14 | 43%
15 | 32%
16 | 31%
17 | 25%
18 | 21%
19 | 10%
20 | 1%
21 | -8%
22 | -85%

Table 8 Summary Statistics on Number of HAE Attacks in the Randomized, Placebo-Controlled, Crossover, Routine Prophylaxis Trial.
Statistics | CINRYZE N=22 | Placebo N=22
Mean | 6.1 | 12.7
SD | 5.4 | 4.8
Median | 6 | 13.5
Min | 0 | 6
Max | 17 | 22

Table 9 Summary of Generalized Estimating Equation (GEE) Analysis Results (p-value) in the Randomized, Placebo-Controlled, Crossover, Routine Prophylaxis Trial.
Effect Assessed | CINRYZE
Treatment Effect | <0.0001
Sequence Effect | 0.3347
Period Effect | 0.3494

Subjects treated with CINRYZE had a 66% reduction in days of swelling (p<0.0001) and decreases in the average severity of attacks (p=0.0006) and the average duration of attacks (p=0.0023), as shown in Table 10.

Table 10 Secondary Efficacy Outcomes in the Randomized, Placebo-Controlled, Crossover, Routine Prophylaxis Trial.
Parameters | CINRYZE N=22 | Placebo N=22 | 95% Confidence Interval for Treatment Effect (Placebo minus CINRYZE)
Mean Severity of HAE Attacks (Score from 1 to 3) [1=mild; 2=moderate; and 3=severe] (SD) | 1.3 (0.85) | 1.9 (0.36) | 0.58 [p<0.01] (0.19, 0.97)
Mean Duration of HAE Attacks (Days) (SD) | 2.1 (1.13) | 3.4 (1.4) | 1.23 (0.49, 1.96)
Days of Swelling (SD) | 10.1 (10.73) | 29.6 (16.9) | 19.5 (11.94, 27.06)

The safety and efficacy of CINRYZE (500 U and 1,000 U) for the prevention of HAE attacks and the reduction of the severity and requirement for acute treatment was demonstrated in a randomized, single-blind, multicenter, dose-ranging cross-over study of 12 pediatric subjects aged 7 to 11 years.

During the 12-week study period, a greater reduction in the normalized number of angioedema attacks per month was observed with 1,000 U CINRYZE compared to 500 U CINRYZE (p=0.03). When compared to the baseline observational period, a reduction in the normalized number of angioedema attacks was observed for both CINRYZE 500 U and CINRZYE 1,000 U (mean absolute reduction in number of HAE attacks: 2.6, 3.0 respectively; mean percent reduction in HAE attacks: 71.1% and 84.5%, respectively). In addition, both doses lessened the severity of attacks and reduced the use of acute treatment compared with baseline. Refer to Table 11 and Table 12 for the additional parameters.

Table 11 Time-Normalized [Scaled normalized score is expressed as the score per month (× 30.4, number of days per month)] Number of HAE Attacks per Month during Observation Period and 12 Week Treatment Period with CINRYZE 500 U and 1,000 U.
Parameters | Observation Period N = 12 | CINRYZE 500 U* N = 12 | CINRYZE 1,000 U* N = 12
Mean (SD) | 3.7 (3.15) | 1.2 (1.53) | 0.7 (1.35)
Min, Max | 1.0, 11.8 | 0.0, 5.6 | 0.0, 4.8
Median | 2.2 | 0.8 | 0.4

Table 12 Difference in Time-Normalized Number of HAE Attacks per Month for CINRYZE 500 U and 1,000 U 12-Week Treatment Periods from Observation Period.
Parameters | CINRYZE 500 U N = 12 | CINRYZE 1,000 U N = 12
Mean (SD) | -2.6 (2.88) | -3.0 (2.87)
90% CI | (-4.1, -1.1) | (-4.5, -1.5)
Mean % reduction | 71.1% | 84.5%
Median % reduction | 76.2% | 87.4%

15 REFERENCES

1. Horstick, G et al, 2001. Circulation 104:3125-3131.
2. Davis AE, The pathophysiology of hereditary angioedema. Clin Immunol. 2005; 114:3-9.

16 HOW SUPPLIED/STORAGE AND HANDLING

How Supplied

CINRYZE 500 IU is a lyophilized powder supplied in the following presentation.

One single-dose glass vial with one Sterile Water for Injection, USP

- 1 vacuum-sealed single-dose glass vial
- 5 mL of Sterile Water for Injection USP
- Vial NDC number: 42227-081-01
- Carton NDC number: 42227-083-01

Storage and Handling

- It is packaged for sale, and is stable for the period stated on the vial and carton label when stored at 36°F to 77°F (2°C to 25°C)
- Do not freeze.
- Store the vial in the original carton to protect it from light.
- Do not use beyond the expiration date on the vial of CINRYZE.

17 PATIENT COUNSELING INFORMATION

See FDA-approved patient labeling (Information for the Patient).

- Inform patients to immediately report the following to their physician:
  - Signs of allergic-type hypersensitivity reactions including hives (itchy white elevated patches), tightness of the chest, wheezing, hypotension and anaphylaxis [see Warnings and Precautions (5.1)]. Advise patients to discontinue use of CINRYZE and contact their physicians if these symptoms occur.
  - Signs of a thromboembolic event including pain and/or swelling of an arm or leg with warmth over the affected area, discoloration of an arm or leg, unexplained shortness of breath, chest pain or discomfort that worsens on deep breathing, unexplained rapid pulse, numbness, or weakness on one side of the body.
- Advise patients with known risk factors for thromboembolic events that they may be at increased risk for these events.
- Advise female patients to notify their physician if they become pregnant or intend to become pregnant during their routine prevention with CINRYZE.
- Advise patients to notify their physician if they are breastfeeding or plan to breastfeed.
- Based on their current regimen, advise patients to bring an adequate supply of CINRYZE for routine prevention when traveling.
- Advise patient that, because CINRYZE is made from human blood, it may carry a risk of transmitting infectious agents, e.g. viruses, and, theoretically, the Creutzfeldt-Jakob disease (CJD) agent [see Warnings and Precautions (5.3), see Description (11)]. The risk of transmitting disease has been reduced, but not eliminated, by carefully selecting blood donors, testing donors for infections, and inactivating or removing most viruses during the manufacturing process.
- Inform patients of the risks and benefits of CINRYZE before prescribing or administering to the patient.

FDA-Approved Patient Labeling

Information for the Patient

CINRYZE® (SIN-rise)

(C1 esterase inhibitor [human])

This leaflet summarizes important information about CINRYZE. Please read it carefully before using CINRYZE and each time you get a refill. There may be new information. This information does not take the place of talking with your healthcare provider, and it does not include all of the important information about CINRYZE. If you have any questions after reading this, ask your healthcare provider.

Do not attempt to self-administer unless you have been taught how by your healthcare provider.

What is CINRYZE?

CINRYZE is an injectable medicine that is used to help prevent swelling and/or painful attacks in children (6 years of age and older), teenagers and adults with Hereditary Angioedema (HAE). HAE is caused by the decreased functioning of a protein called C1 esterase inhibitor, that is present in your blood and helps control inflammation (swelling) and parts of the immune system. CINRYZE contains C1 esterase inhibitor. Before you can inject CINRYZE into your vein (intravenous injection), you must dissolve the CINRYZE powder using Sterile Water for Injection, USP. You can get supplies, including Sterile Water for Injection, USP from your pharmacist.

Who should not use CINRYZE?

You should not use CINRYZE if you have had life-threatening immediate hypersensitivity reactions, including anaphylaxis, to the product.

What should I tell my healthcare provider before using CINRYZE?

Tell your healthcare provider about all of your medical conditions, including if you

- have an indwelling catheter/access device in one of your veins.
- have a history of blood clots, heart disease, or stroke.
- are taking birth control pills or androgens.
- are pregnant or planning to become pregnant. It is not known if CINRYZE can harm your unborn baby.
- are breastfeeding or plan to breastfeed. It is not known if CINRYZE passes into your milk and if it can harm your baby.

Tell your healthcare provider and pharmacist about all of the medicines you take, including all prescription and non-prescription medicines such as over-the-counter medicines, supplements, or herbal remedies.

What are the possible side effects of CINRYZE?

Allergic reactions may occur with CINRYZE. Call your healthcare provider or get emergency support services right away if you have any of the following symptoms:

- wheezing
- difficulty breathing
- chest tightness
- turning blue (look at lips and gums)
- fast heartbeat
- swelling of the face
- faintness
- rash
- hives

Serious blood clots may occur with CINRYZE. Call your healthcare provider or get emergency support services right away if you have any of the following symptoms:

- pain and/or swelling of an arm or leg with warmth over the affected area
- discoloration of an arm or leg
- unexplained shortness of breath
- chest pain or discomfort that worsens on deep breathing
- unexplained rapid heart rate
- numbness or weakness on one side of the body

The most common side effects seen with CINRYZE were headache, nausea, rash, and vomiting.

These are not all the possible side effects of CINRYZE.

Tell your healthcare provider about any side effect that bothers you or that does not go away. You can also report side effects to Takeda Pharmaceuticals U.S.A., Inc. [1-877-TAKEDA-7 (1-877-825-3327)] or the FDA at 1-800-FDA-1088.

You can ask your healthcare provider for information that is written for healthcare providers.

How should I store CINRYZE?

Do not freeze CINRYZE.

Store CINRYZE in a refrigerator or at room temperature between 36°F to 77°F (2°C to 25°C).

Keep CINRYZE in the original carton to protect it from light.

Do not use CINRYZE after the expiration date on the vial.

What else should I know about CINRYZE?

Medicines are sometimes prescribed for purposes other than those listed here. Do not use CINRYZE for a condition for which it is not prescribed. Do not share CINRYZE with other people, even if they have the same symptoms that you have.

Because CINRYZE is made from human blood, it may carry a risk of transmitting infectious agents, e.g., viruses, and, theoretically, the Creutzfeldt-Jakob (CJD) agent.

This leaflet summarizes the most important information about CINRYZE. If you would like more information, talk to your healthcare provider. You can ask your healthcare provider or pharmacist for information about CINRYZE that was written for healthcare professionals.

Instructions for Use

CINRYZE® (SIN-rise)

(C1 esterase inhibitor [human])

Do not attempt to self-administer unless you have been taught how by your healthcare provider.

See the step-by-step instructions for injecting CINRYZE at the end of this leaflet. You should always follow the specific instructions given by your healthcare provider. The steps listed below are general guidelines for using CINRYZE. If you are unsure of the steps, please call your healthcare provider or pharmacist before using.

Call your healthcare provider right away if swelling is not controlled after using CINRYZE.

Your healthcare provider will prescribe the dose that you should take.

Call your healthcare provider if you take too much CINRYZE.

Call your healthcare provider if you miss a dose of CINRYZE.

Talk to your healthcare provider before traveling. You should plan to bring enough CINRYZE for your treatment during this time.

Preparation of CINRYZE

Always wash your hands before doing the following steps. Try to keep everything clean and germ-free while you are reconstituting CINRYZE. Once you open the vials, you should finish preparing CINRYZE as soon as possible. This will help to keep them germ-free.

CINRYZE is a Freeze-Dried powder that is supplied in a vacuum-sealed vial.

Note: One vial of CINRYZE is required for each 500 IU dose. Two vials of CINRYZE are required for each 1,000 IU dose. If two vials are required, you should reconstitute both vials according to steps 1 through 6.

Your healthcare provider may decide you require higher doses of CINRYZE. You should always follow the specific instructions given by your healthcare provider.

1. Let the vial of CINRYZE and the vial of Sterile Water for Injection, USP (diluent) reach room temperature.
2. Remove the cap from the vial of CINRYZE and Sterile Water for Injection, USP (diluent) vial to show the center part of the rubber stopper (Figure 6).
  Figure 6
3. Wipe the top of each vial with an alcohol wipe or swab and allow it to dry. Do not blow on the stopper to dry it faster. Place each vial on a flat surface. After cleaning, do not touch the rubber stopper with your hand or allow it to touch any surface (Figure 7).
  Figure 7

Note: Diluent vial must be penetrated before the CINRYZE vial to prevent loss of vacuum.

4. Remove the protective covering from the top of the Mix2Vial transfer device package (Figure 8). Do not remove the device from the package. Place the Sterile Water for Injection, USP (diluent) vial on a flat surface, and place the blue end of the Mix2Vial transfer device over it, pushing down until the spike penetrates the rubber stopper and the device snaps in place. Mix2Vial transfer device must be positioned completely upright before penetrating the rubber stopper (Figure 9). Remove the plastic package and discard it. Take care not to touch the exposed end of the device (Figure 10).
  Figure 8
  Figure 9
  Figure 10
5. Place the vial of CINRYZE on a flat surface. Turn the diluent vial containing 5 mL of Sterile Water for Injection, USP, upside-down and insert the clear end of the Mix2Vial transfer device into the vial of CINRYZE, pushing down until the spike penetrates the rubber stopper and the device snaps in place (Figure 11). The Mix2Vial transfer device must be positioned completely upright before penetrating the rubber stopper. The Sterile Water for Injection, USP, will automatically flow into the vial of CINRYZE because the vacuum in the vial will draw the Sterile Water for Injection, USP, into the vial of CINRYZE. If this does not happen, do not use the product (Figure 12).
  Figure 11
  Figure 12
6. Once all the Sterile Water for Injection, USP, is in the CINRYZE vial, gently swirl (do not shake) the vial of CINRYZE until all the powder is dissolved (Figure 13). Disconnect the Sterile Water for Injection, USP vial by turning it counterclockwise (Figure 14).

Do not remove the clear end of the Mix2Vial transfer device from the vial of CINRYZE.

Figure 13

Figure 14

Look at the final solution before using it to make sure that CINRYZE is completely dissolved. The solution should be clear with no evidence of cloudiness. Reconstituted solution should be colorless to slightly blue. Do not use if solution is cloudy or otherwise discolored and call Takeda Pharmaceuticals [1-877-TAKEDA-7 (1-877-825-3327)] for further instructions.

One vial of dissolved CINRYZE contains 5 mL of C1 esterase inhibitor at a concentration of 100 IU/mL. Prepare one vial of CINRYZE for one 500 IU dose. Prepare two vials of CINRYZE for one 1,000 IU dose. If preparing two vials, repeat steps 1-6 using a new Mix2Vial transfer device.

Do not reuse the Mix2Vial transfer device. CINRYZE should be administered within 3 hours of reconstitution.

7. Utilizing a sterile, disposable 10 mL syringe, draw back the plunger to allow approximately 5 mL of air into the syringe. Use of a silicone-free syringe is recommended (Figure 15).
  Figure 15
8. Attach the syringe onto the clear end of the Mix2Vial transfer device by turning it clockwise (Figure 16).
  Figure 16
9. Turn the vial of CINRYZE upside down, inject air into the vial (Figure 17). Slowly pull as much dissolved CINRYZE as possible into the syringe (Figure 18). While holding the vial upside down, detach the syringe from the vial by turning it counterclockwise and releasing it from the Mix2Vial transfer device (Figure 19). Remove any air bubbles by gently tapping the syringe with your finger and slowly pushing the air out of the syringe (Figure 20).
  Figure 17
  Figure 18
  Figure 19
  Figure 20
- If preparing a 1,000 IU dose (two vials), repeat steps 7 to 9 above with a second vial of CINRYZE to make one complete dose of 10 mL (Figure 21, Figure 22, Figure 23, Figure 24).
  Figure 21
  Figure 22
  Figure 23
  Figure 24
10. Dispose of the vial(s) with the Mix2Vial transfer device attached to them.

CINRYZE should be administered at room temperature promptly after preparation in the syringe.

SELF ADMINISTRATION (Intravenous Injection)

Your healthcare provider will teach you how to safely administer CINRYZE. It is important that CINRYZE is injected directly into a superficial vein and not injected into surrounding tissues and not injected into an artery. Once you learn how to self-administer, you can follow the instructions in this insert.

1. Attach a needle or infusion set with a winged adapter to the syringe containing the dissolved CINRYZE solution. Fill the tubing with dissolved CINRYZE by gently pushing the plunger of the syringe. Be careful not to spill the dissolved CINRYZE. This process replaces the air in the tubing with dissolved CINRYZE.
2. Apply a tourniquet and prepare the injection site by wiping the skin well with an alcohol swab (Figure 25).
  Figure 25
3. As instructed by your healthcare provider:

- Insert the butterfly needle of the infusion set tubing into your vein.
- Remove the tourniquet.
- Make sure that the needle is in a vein.
- Inject the dissolved CINRYZE product slowly over five minutes for a 500 IU dose, or over ten minutes for a 1,000 IU dose (approximately 1mL/min) (Figure 26).
  Figure 26

4. After infusing CINRYZE, remove the infusion set and discard. Cover infusion site with an adhesive bandage (Figure 27). The amount of drug product left in the infusion set will not affect your treatment. Dispose of all unused solution, the empty vial(s), and the used needles and syringe in an appropriate container used for throwing away waste that might hurt others if not handled properly.
  Figure 27

It is a good idea to record the lot number from the CINRYZE vial label every time you use CINRYZE.

This Patient Package Insert has been approved by the U.S. Food and Drug Administration.

Manufactured by:

Takeda Pharmaceuticals U.S.A., Inc.
Cambridge, MA 02142

U.S. License Number: 1898

Revised: 11/2024

Mix2Vial® and the exterior configuration of the drug delivery device are trademarks of West Pharmaceutical Services, Inc., or one of its subsidiaries, and are used with permission.

CINRYZE and are registered trademarks of ViroPharma Biologics LLC.

Takeda and are registered trademarks of Takeda Pharmaceutical Company Limited.

©2024 Takeda Pharmaceuticals U.S.A., Inc. All rights reserved.

Revised: 11/2024

PRINCIPAL DISPLAY PANEL - 500 IU Vial Label

FOR INTRAVENOUS INJECTION

C1 esterase inhibitor (human)

CINRYZE®
500 IU

NDC 42227-081-01

Reconstitute with 5 mL Sterile Water for Injection, USP.
Use entire contents within 3 hours of reconstitution.
Discard any unused content.
Single-dose vial • Rx only • US License No. 1898

Manufactured by
Takeda Pharmaceuticals U.S.A., Inc.
Cambridge, MA 02142

0762843

PRINCIPAL DISPLAY PANEL - Kit Carton

NDC 42227-083-01

C1 esterase inhibitor
(human)

CINRYZE®

500 IU

FOR INTRAVENOUS INJECTION

Contains: One single-dose vial of 500 IU
Cinryze and one 5 mL vial of Sterile Water for
Injection, USP.

Rx only

Derived from human plasma.
Plasma derived products may carry a risk of
transmitting infectious agents.
Refer to the package insert for all
Warnings and Precautions.

Takeda